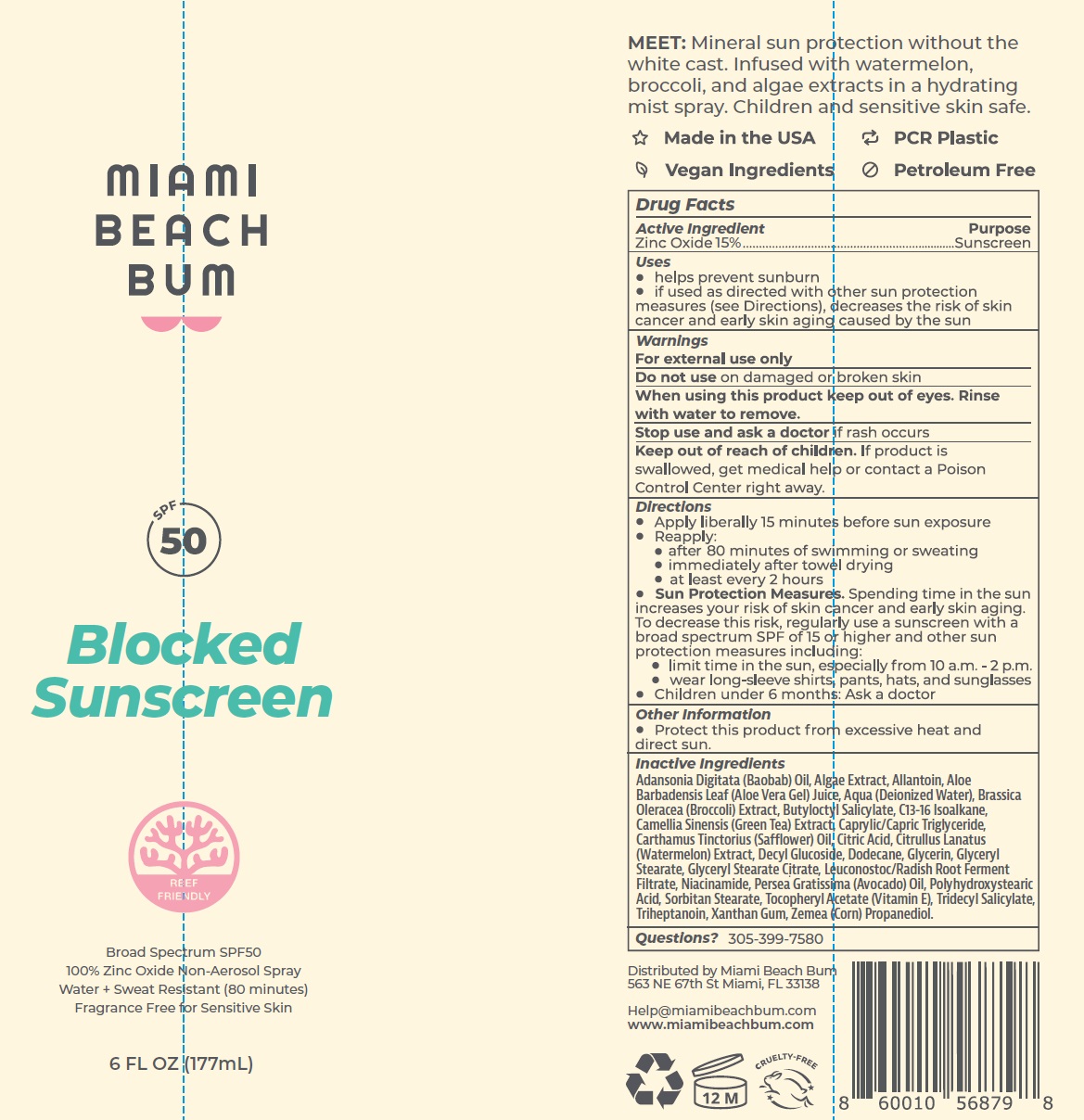 DRUG LABEL: MIAMI BEACH BUM SPF-50 Blocked Sunscreen
NDC: 82812-448 | Form: LIQUID
Manufacturer: MIAMI BEACH BUM
Category: otc | Type: HUMAN OTC DRUG LABEL
Date: 20240207

ACTIVE INGREDIENTS: ZINC OXIDE 150 mg/1 mL
INACTIVE INGREDIENTS: ADANSONIA DIGITATA SEED OIL; ALLANTOIN; ALOE VERA LEAF; WATER; BROCCOLI; BUTYLOCTYL SALICYLATE; C13-16 ISOPARAFFIN; GREEN TEA LEAF; MEDIUM-CHAIN TRIGLYCERIDES; SAFFLOWER; CITRIC ACID MONOHYDRATE; WATERMELON; DECYL GLUCOSIDE; DODECANE; GLYCERIN; GLYCERYL MONOSTEARATE; GLYCERYL STEARATE CITRATE; LEUCONOSTOC/RADISH ROOT FERMENT FILTRATE; NIACINAMIDE; AVOCADO OIL; SORBITAN MONOSTEARATE; .ALPHA.-TOCOPHEROL ACETATE; TRIDECYL SALICYLATE; TRIHEPTANOIN; XANTHAN GUM; CORN

MIAMI BEACH BUM SPF-50 Blocked Sunscreen

Active Ingredient

Zinc Oxide 15%

Purpose

Sunscreen

Uses

- helps prevent sunburn
- if used as directed with other sun protection measures (see Directions), decreases the risk of skin cancer and early skin aging caused by the sun

Warnings

For external use only

Do not use

on damaged or broken skin

When using this product

keep out of eyes. Rinse with water to remove.

Stop use and ask a doctor

if rash occurs

Keep out of reach of children.

If product is swallowed, get medical help or contact a Poison Control Centre right away.

Directions

- Apply liberally 15 minutes before sun exposure
- Reapply:
- after 80 minutes of swimming or sweating
- immidiately after towel drying
- at least every 2 hours
- S un Protection Measures. Spending time in the sun increases your risk of skin cancer and early skin aging. To decrease this risk, regularly use a sunscreen with a broad spectrum SPF of 15 or higher and other sun protection measures including:
- limit time in the sun, especially from 10 a.m. -2 p.m.
- wear long-sleeve shirts, pants, hats, and sunglasess
- Children under 6 months: Ask a doctor

Other Information

- Protect this product from excessive heat and direct sun.

Inactive Ingredients

Adansonia Digitata (Baobab) Oil, Algae Extract, Allantoin, Aloe Barbadensis Leaf (Aloe Vera Gel) Juice, Aqua (Deionized Water), Brassica Oleracea (Broccoli) Extract, Butyloctyl Salicylate, C13-16 Isoalkane, Camellia Sinensis (Green tea) Etract, Caprylic/Capric Triglyceride, Carthamus Tinctorious (safflower) oil, Citric Acid, Citrullus Lanatus (Watermelon) Extract, Decyl Glucoside, Dodecane, Glycerin, Glyceryl Stearate, Glyceryl Stearate Citrate, Leuconostoc/Radish Root Ferment Filtrate, Niacinamide, Persea Gratissima (Avocado) Oil, Polyhydroxystearic Acid, Sorbitan Stearate, Tocopheryl Acetate (Vitamin E), Tridecyl Salicylate, Triheptanoin, Xanthan Gum, Zemea (Corn) Propanediol.

Questions?

305-399-7580